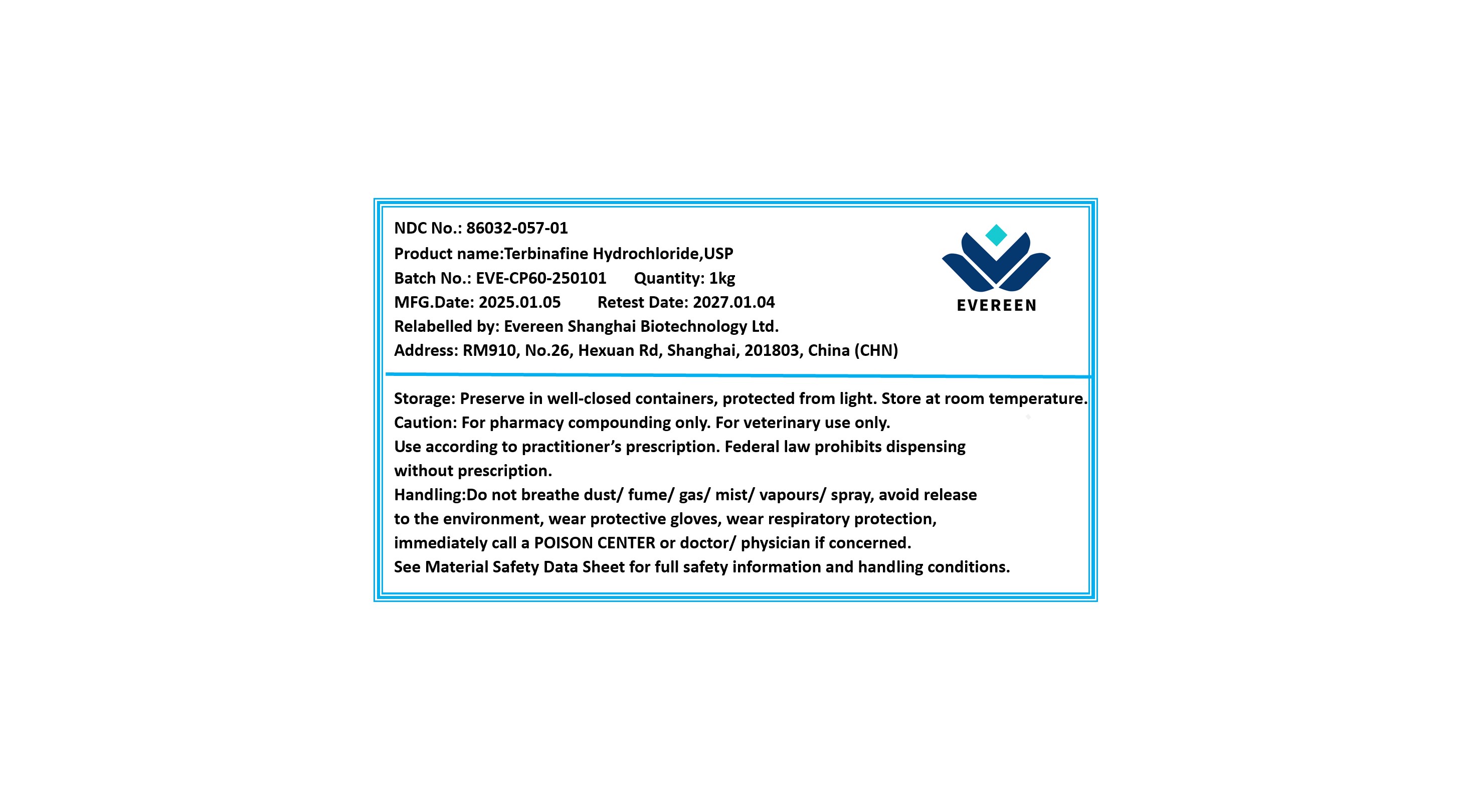 DRUG LABEL: Terbinafine Hydrochloride
NDC: 86032-057 | Form: POWDER
Manufacturer: Evereen Shanghai Biotechnology Ltd.
Category: other | Type: BULK INGREDIENT - ANIMAL DRUG
Date: 20250821

ACTIVE INGREDIENTS: TERBINAFINE HYDROCHLORIDE 1 g/1 g

Terbinafine Hydrochloride